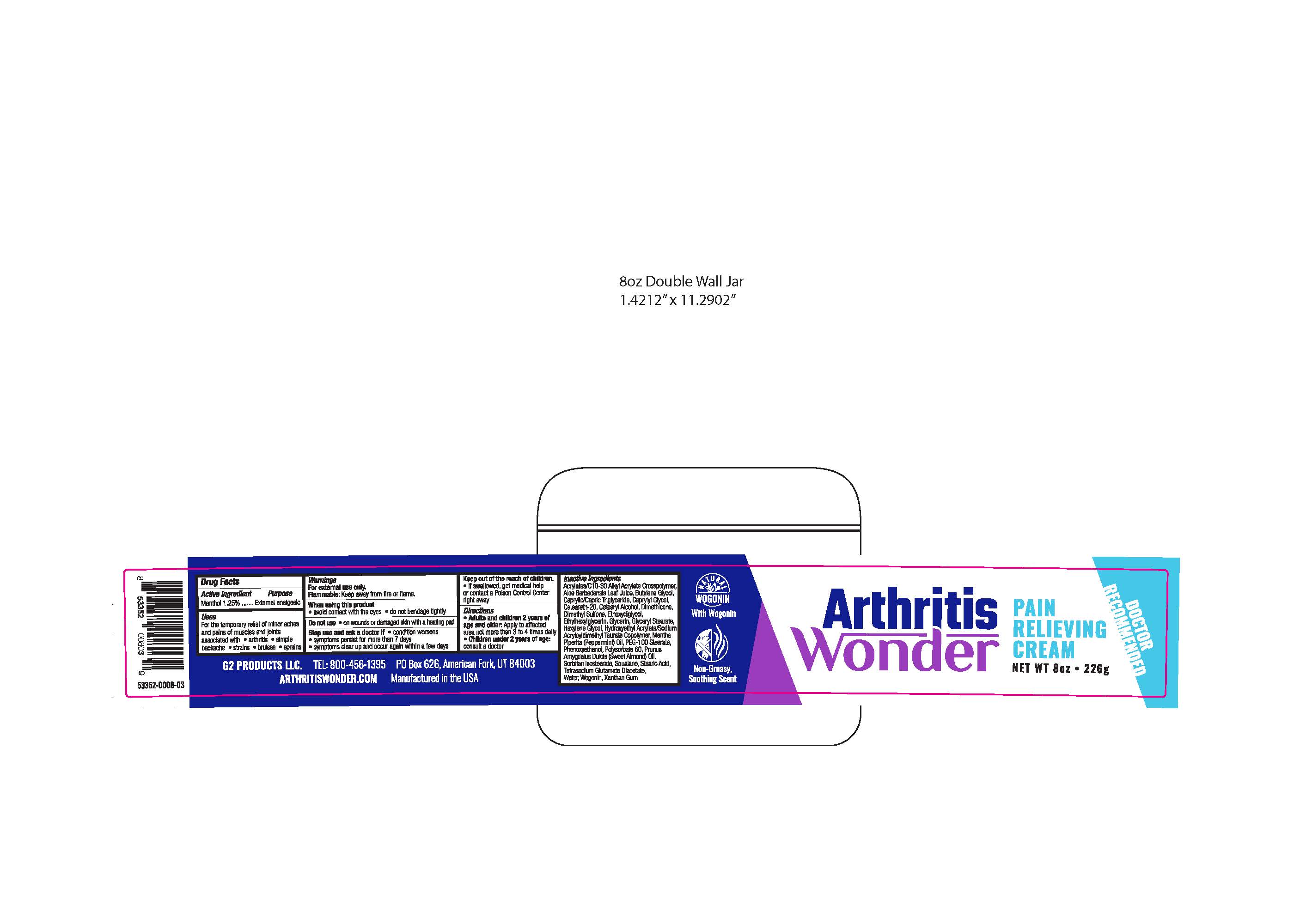 DRUG LABEL: Arthritis Wonder
NDC: 71893-101 | Form: CREAM
Manufacturer: G2 Products LLC
Category: otc | Type: HUMAN OTC DRUG LABEL
Date: 20200326

ACTIVE INGREDIENTS: MENTHOL 1.4125 g/113 g
INACTIVE INGREDIENTS: DIMETHICONE; HYDROXYETHYL ACRYLATE/SODIUM ACRYLOYLDIMETHYL TAURATE COPOLYMER (45000 MPA.S AT 1%); PEG-100 STEARATE; PHENOXYETHANOL; DIETHYLENE GLYCOL MONOETHYL ETHER; GLYCERIN; HEXYLENE GLYCOL; PEPPERMINT OIL; POLYSORBATE 60; SORBITAN ISOSTEARATE; TETRASODIUM GLUTAMATE DIACETATE; ETHYLHEXYLGLYCERIN; WATER; WOGONIN; XANTHAN GUM; CARBOMER INTERPOLYMER TYPE A (55000 CPS); ALOE VERA LEAF; BUTYLENE GLYCOL; MEDIUM-CHAIN TRIGLYCERIDES; CAPRYLYL GLYCOL; POLYOXYL 20 CETOSTEARYL ETHER; CETOSTEARYL ALCOHOL; DIMETHYL SULFONE; GLYCERYL MONOSTEARATE; ALMOND OIL; SQUALANE; STEARIC ACID

Arthritis Wonder

Active ingredient

Menthol 1.25%

Purpose

External analgesic

Uses

For the temporary relief of minor aches and pains of muscles and joints associated with ● arthritis ● simple backache ● strains ● bruises ● sprains

Warnings

For external use only.

Flammable: Keep away from fire or flame.

When using this product

• avoid contact with the eyes • do not bandage tightly

Do not use

● on wounds or damaged skin with a heating pad

Stop use and ask a doctor if

• condition worsens • symptoms persist for more than 7 days • symptoms clear up and occur again within a few days

Keep out of the reach of children

If swallowed, get medical help or contact a Poison Control Center right away

Directions

• Adults and children 2 years of age and older: Apply to affected area not more than 3 to 4 times daily • Children under 2 years of age: consult a doctor

Inactive ingredients:

Acrylates/C10-30 Alkyl Acrylate Crosspolymer, Aloe Barbadensis Leaf Juice, Butylene Glycol, Caprylic/Capric Triglyceride, Caprylyl Glycol, Ceteareth-20, Cetearyl Alcohol, Dimethicone, Dimethyl Sulfone, Ethoxydiglycol, Ethylhexylglycerin, Glycerin, Glyceryl Stearate, Hexylene Glycol, Hydroxyethyl Acrylate/Sodium Acryloyldimethyl Taurate Copolymer, Mentha Piperita (Peppermint) Oil, PEG-100 Stearate, Phenoxyethanol, Polysorbate 60, Prunus Amygdalus Dulcis (Sweet Almond) Oil, Sorbitan Isostearate, Squalane, Stearic Acid, Tetrasodium Glutamate Diacetate, Water, Wogonin, Xanthan Gum